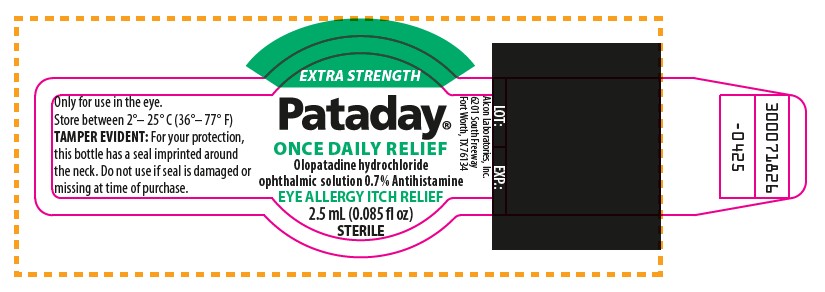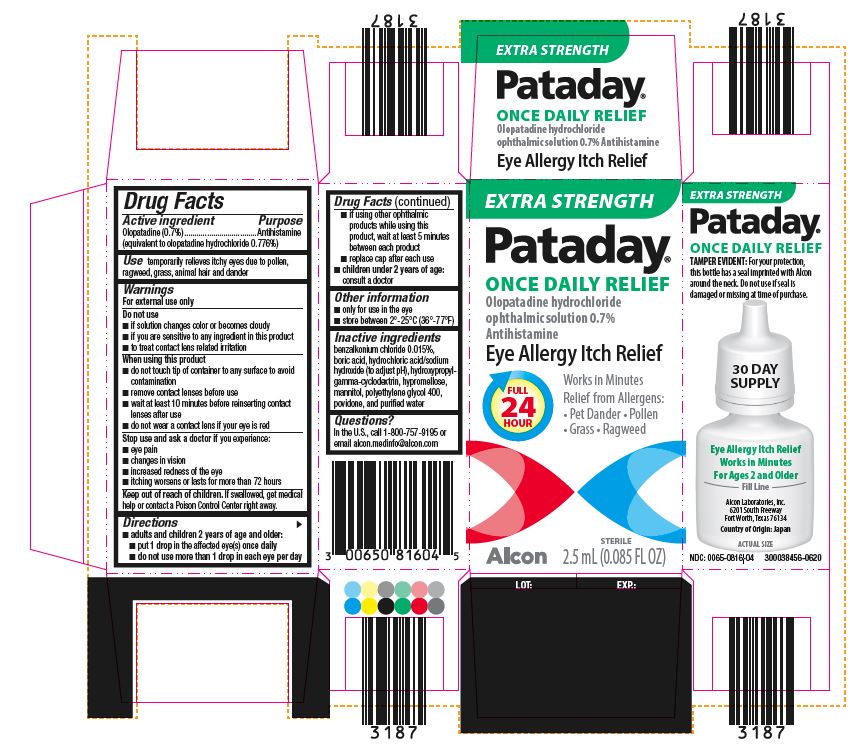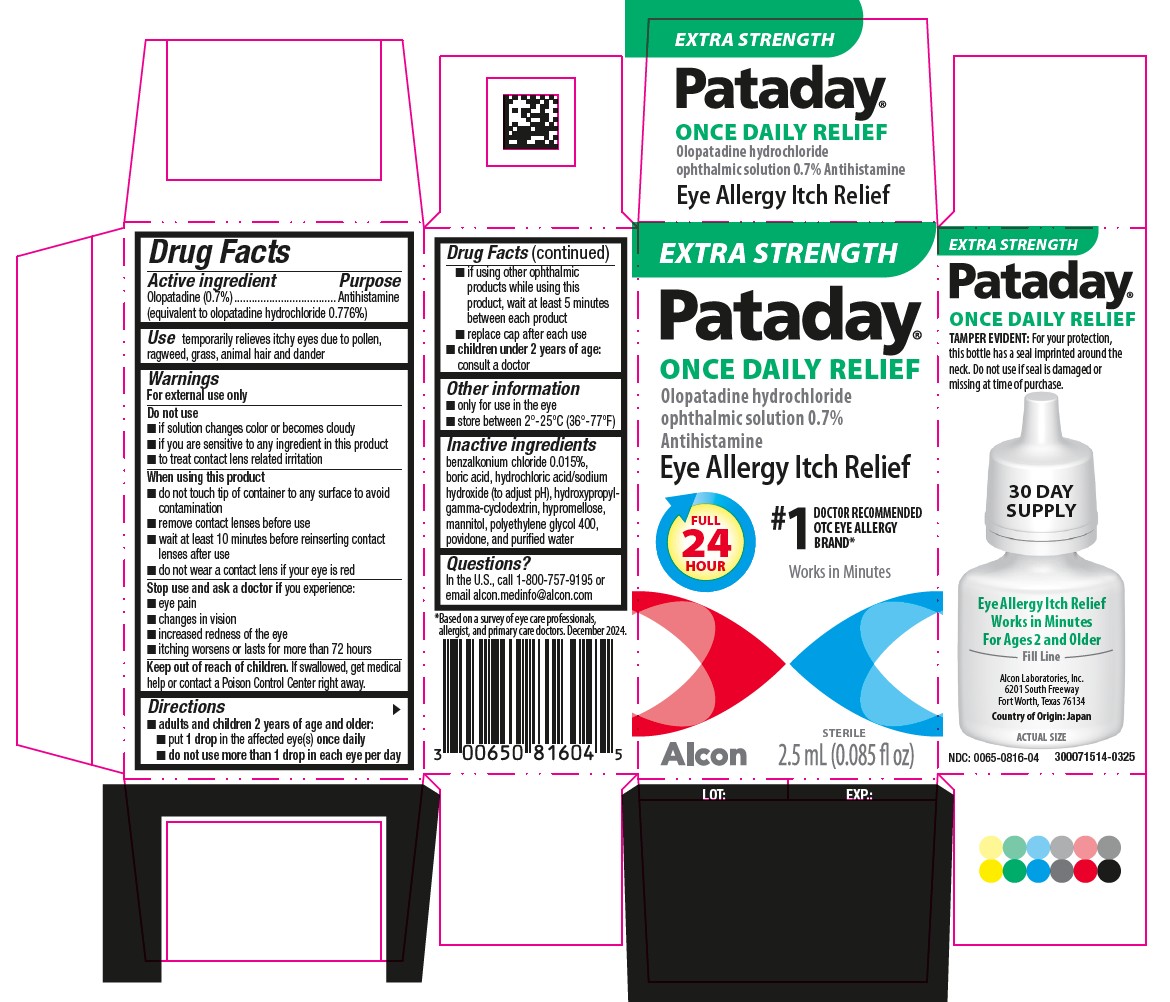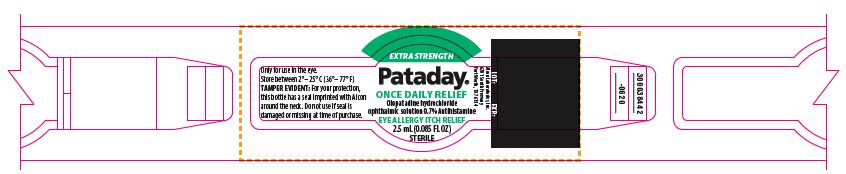 DRUG LABEL: PATADAY ONCE DAILY RELIEF
NDC: 0065-0816 | Form: SOLUTION
Manufacturer: Alcon Laboratories, Inc.
Category: otc | Type: HUMAN OTC DRUG LABEL
Date: 20260120

ACTIVE INGREDIENTS: Olopatadine Hydrochloride 7 mg/1 mL
INACTIVE INGREDIENTS: Benzalkonium Chloride; Boric Acid; Hydrochloric Acid; Sodium Hydroxide; Hydroxypropyl .Gamma.-Cyclodextrin; Hypromellose, Unspecified; Mannitol; Polyethylene Glycol 400; Povidone, Unspecified; Water

Drug Facts

ACTIVE INGREDIENT

Active Ingredients | Purpose
Olopatadine (0.7%) (equivalent to olopatadine hydrochloride 0.776%) | Antihistamine

INDICATIONS AND USAGE

Use temporarily relieves itchy eyes due to pollen, ragweed, grass, animal hair and dander

Warnings
For external use only

Do not use

- if solution changes color or becomes cloudy
- if you are sensitive to any ingredient in this product
- to treat contact lens related irritation

When using this product

- do not touch tip of container to any surface to avoid contamination
- remove contact lenses before use
- wait at least 10 minutes before reinserting contact lenses after use
- do not wear a contact lens if your eye is red

Stop use and ask a doctor if you experience:

- eye pain
- changes in vision
- increased redness of the eye
- itching worsens or lasts for more than 72 hours

Keep out of reach of children. If swallowed, get medical help or contact a Poison Control Center right away.

Directions

- adults and children 2 years of age and older:
  - put 1 drop in the affected eye(s) once daily
  - do not use more than 1 drop in each eye per day
  - if using other ophthalmic products while using this product, wait at least 5 minutes between each product
  - replace cap after each use
- children under 2 years of age: consult a doctor

Other information

- only for use in the eye
- store between 2°-25°C (36°-77°F)

Inactive ingredients

benzalkonium chloride 0.015%, boric acid, hydrochloric acid/sodium hydroxide (to adjust pH), hydroxypropylgamma- cyclodextrin, hypromellose, mannitol, polyethylene glycol 400, povidone, and purified water

Questions?

In the U.S., call 1-800-757-9195 or email alcon.medinfo@alcon.com

PRINCIPAL DISPLAY PANEL

EXTRA STRENGTH
Pataday®
ONCE DAILY RELIEF
Olopatadine hydrochloride
ophthalmic solution 0.7%
Antihistamine
Eye Allergy Itch Relief
FULL 24 HOUR
Works in Minutes
Relief from Allergens:
• Pet Dander
• Pollen
• Grass
• Ragweed
Alcon
STERILE
2.5 mL (0.085 FL OZ)
EXTRA STRENGTH
Pataday®
ONCE DAILY RELIEF
TAMPER EVIDENT: For your protection, this bottle has a seal imprinted with Alcon around the neck. Do not use if seal is damaged or missing at time of purchase.
30 DAY SUPPLY
Eye Allergy Itch Relief
Works in Minutes
For Ages 2 and Older
________Fill Line________
Alcon Laboratories, Inc.
6201 South Freeway
Fort Worth, Texas 76134
Country of Origin: Japan
ACTUAL SIZE
NDC: 0065-0816-04
300038456-0620
LOT: EXP.:
3187

EXTRA STRENGTH
Pataday®
ONCE DAILY RELIEF
Olopatadine hydrochloride
ophthalmic solution 0.7% Antihistamine
2.5 mL (0.085 FL OZ)
STERILE
Only for use in the eye.
Store between 2°– 25° C (36°– 77° F)
TAMPER EVIDENT: For your protection, this bottle has a seal imprinted with Alcon around the neck. Do not use if seal is damaged or missing at time of purchase.
Alcon Laboratories, Inc.
6201 South Freeway
Fort Worth, TX 76134
LOT: EXP.:
300038442-0620

EXTRA STRENGTH
Pataday®
ONCE DAILY RELIEF
Olopatadine hydrochloride
ophthalmic solution 0.7%
Antihistamine
Eye Allergy Itch Relief
FULL 24 HOUR
#1 DOCTOR RECOMMENDED
OTC EYE ALLERGY
BRAND*
Works in Minutes
Alcon
STERILE
2.5 mL (0.085 fl oz)
LOT: EXP:
EXTRA STRENGTH
Pataday®
ONCE DAILY RELIEF
Olopatadine hydrochloride
ophthalmic solution 0.7% Antihistamine
Eye Allergy Itch Relief
EXTRA STRENGTH
Pataday®
ONCE DAILY RELIEF
TAMPER EVIDENT: For your protection,
this bottle has a seal imprinted around the
neck. Do not use if seal is damaged or
missing at time of purchase.
30 DAY SUPPLY
Eye Allergy Itch Relief
Works in Minutes
For Ages 2 and Older
________Fill Line________
Alcon Laboratories, Inc.
6201 South Freeway
Fort Worth, Texas 76134
Country of Origin: Japan
ACTUAL SIZE
NDC: 0065-0816-04 300071514-0325
*Based on a survey of eye care professionals,
allergist, and primary care doctors. December 2024.

EXTRA STRENGTH
Pataday®
ONCE DAILY RELIEF
Olopatadine hydrochloride
ophthalmic solution 0.7% Antihistamine
EYE ALLERGY ITCH RELIEF
2.5 mL (0.085 fl oz)
STERILE
Only for use in the eye.
Store between 2°– 25° C (36°– 77° F)
TAMPER EVIDENT: For your protection,
this bottle has a seal imprinted around
the neck. Do not use if seal is damaged or
missing at time of purchase.
Alcon Laboratories, Inc.
6201 South Freeway
Fort Worth, TX 76134
LOT: EXP.:
300071826
-0425